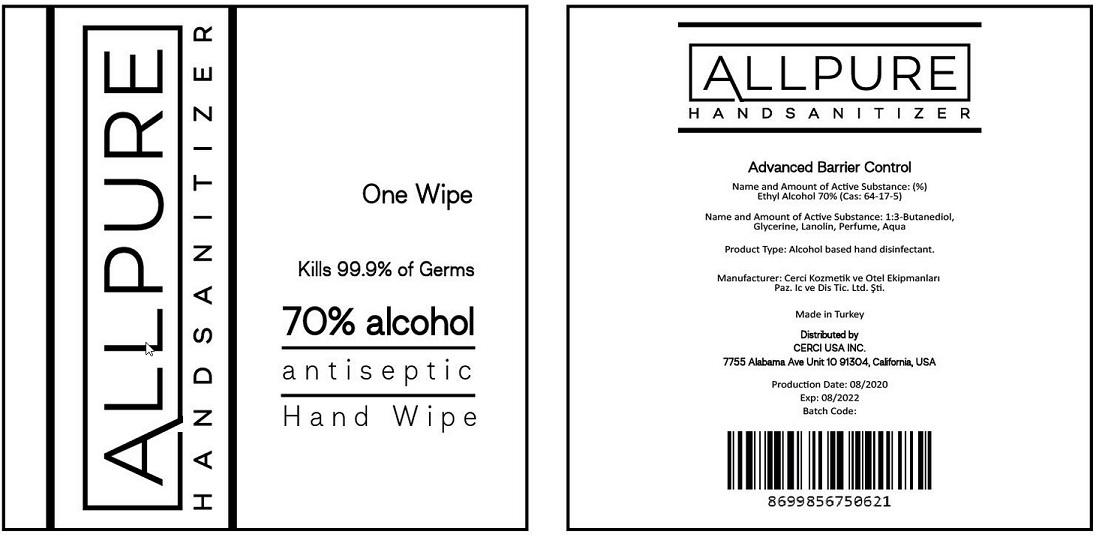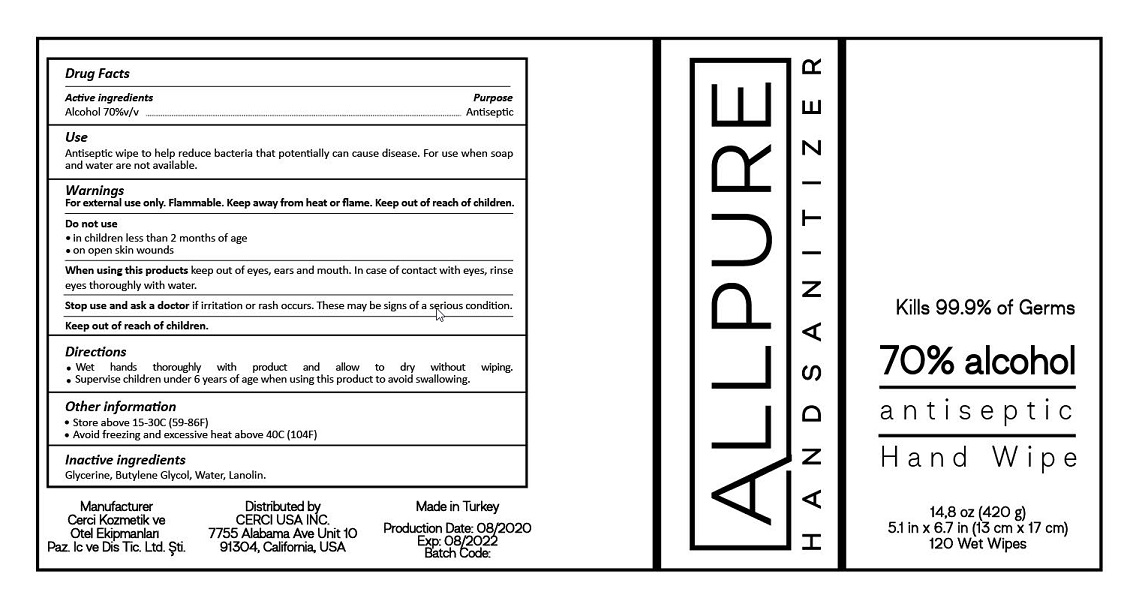 DRUG LABEL: ALLPURE HAND SANITIZER SANITIZING WIPE
NDC: 80176-001 | Form: CLOTH
Manufacturer: CERCI KOZMETIK VE OTEL EKIPMANLARI PAZARLAMA IC VE DIS TICARET LIMITED SIRKETI
Category: otc | Type: HUMAN OTC DRUG LABEL
Date: 20231031

ACTIVE INGREDIENTS: ALCOHOL 70 mL/100 mL
INACTIVE INGREDIENTS: BUTYLENE GLYCOL; GLYCERIN; LANOLIN; WATER

Active Ingredient

Alcohol 70% v/v.

Purpose

Antiseptic

Use

Antiseptic wipe to help reduce bacteria that potentially can cause disease. For use when soap and water are not available.

Warnings

For external use only. Flammable. Keep away from heat or flame. Keep out of reach of children.

Do not use

- in children less than 2 months of age
- on open skin wounds

WHEN USING

When using this productkeep out of eyes, ears, and mouth. In case of contact with eyes, rinse eyes thoroughly with water.

Stop use and ask a doctor ifirritation or rash occurs. These may be signs of a serious condition.

Stop use and ask a doctor ifirritation or rash occurs. These may be signs of a serious condition.

Keep out of reach of children.

Directions

- Wet hands thoroughly with product and allow to dry without wiping.
- Supervise children under 6 years of age when using this product to avoid swallowing.

Other information

- Store between 15-30C (59-86F)
- Avoid freezing and excessive heat above 40C (104F)

Inactive ingredients

Glycerin, Butylene Glycol, Water, Lanolin